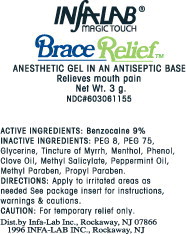 DRUG LABEL: Brace Relief
NDC: 60306-115 | Form: GEL
Manufacturer: InfaLab,Inc
Category: otc | Type: HUMAN OTC DRUG LABEL
Date: 20260116

ACTIVE INGREDIENTS: Benzocaine 9 mg/1 mL
INACTIVE INGREDIENTS: Polyethylene glycol 400; Polyethylene glycol 3350; Glycerin; Myrrh; Menthol; Phenol; Clove Oil; Methyl Salicylate; Peppermint Oil; Methylparaben; Propylparaben

ACTIVE INGREDIENTS:

Benzocaine 9%

INACTIVE INGREDIENTS:

PEG 8, PEG 75, Glycerine, Tincture of Myrrh, Menthol, Phenol, Clove Oil, Methyl Salicylate, Peppermint Oil, Methyl Paraben, Propyl Paraben.

DIRECTIONS:

Apply to irritated areas as needed See package insert for instructions, warnings & cautions.

CAUTION:

For temporary relief only.

Dist.by Infa-Lab Inc., Rockaway, NJ 07866
1996 INFA-LAB INC., Rockaway, NJ

Principal Display Panel – Tube Label

INfALAB®
MAGIC TOUCH

BraceRelief™
ANESTHETIC GEL IN AN ANTISEPTIC BASE
Relieves mouth pain
Net Wt. 3 g.
NDC#603061155